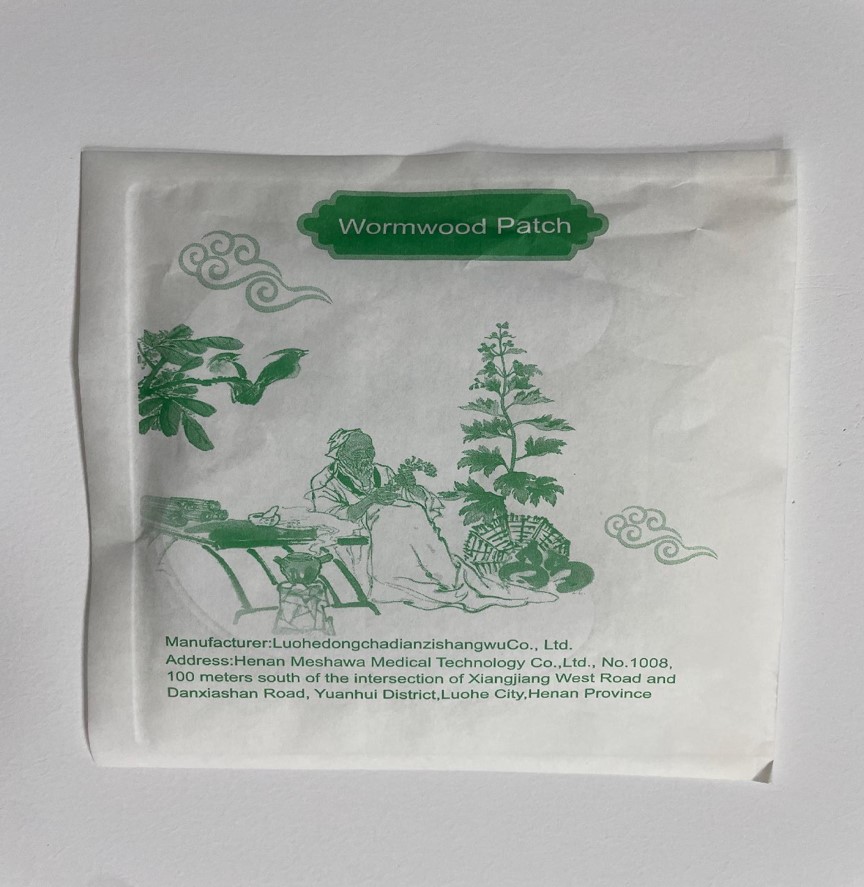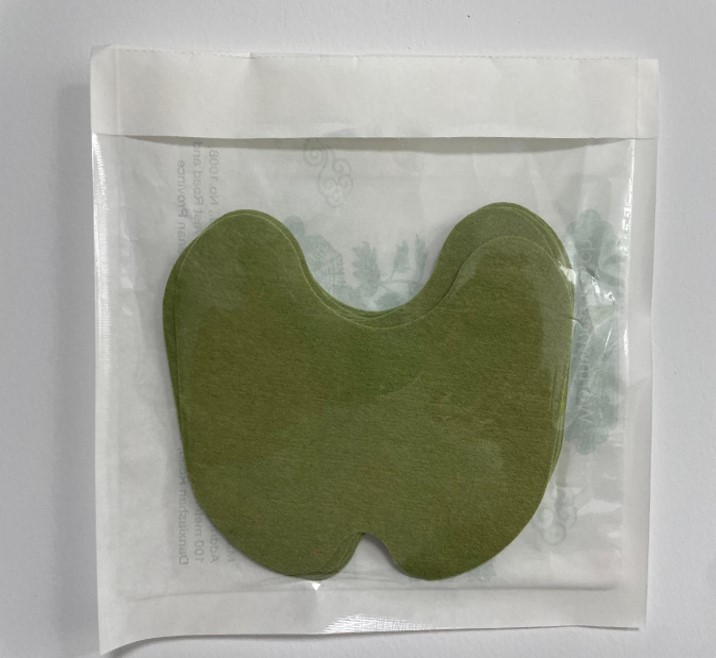 DRUG LABEL: Wormwood patch
NDC: 84971-001 | Form: PATCH
Manufacturer: Luohe Dongcha Ecommerce Co., LTD
Category: otc | Type: HUMAN OTC DRUG LABEL
Date: 20241118

ACTIVE INGREDIENTS: ARTEMISIA ARGYI LEAF 18 g/100 g
INACTIVE INGREDIENTS: PANAX NOTOGINSENG WHOLE; ACONITUM CARMICHAELII WHOLE; GINGER; FRANKINCENSE; SCOLOPENDRA SUBSPINIPES; LYCOPODIUM JAPONICUM WHOLE; CHAMAECYPARIS OBTUSA WHOLE; SAFFLOWER; ANDROCTONUS AUSTRALIS WHOLE; CAMPHOR (NATURAL); BORNEOL; CROAKER, UNSPECIFIED

Wormwood patch

ACTIVE INGREDIENT

Folium artemisia argyi 18%

PURPOSE

Health massage, bodybuilding body

KEEP OUT OF REACH OF CHILDREN SECTION

INDICATIONS AND USAGE

Health massage, bodybuilding body

WARNINGS

For external use only

DOSAGE AND ADMINISTRATION

Remove the patch, tear off the protective film and stick it on the desired area

INACTIVE INGREDIENT

Dried ginger
notoginseng
Scorpio
centipede
Safflower flower
Diaphania japonica
Radix aconiti preparata
Common croaker
frankincense
Herba japonicae
camphor
borneol